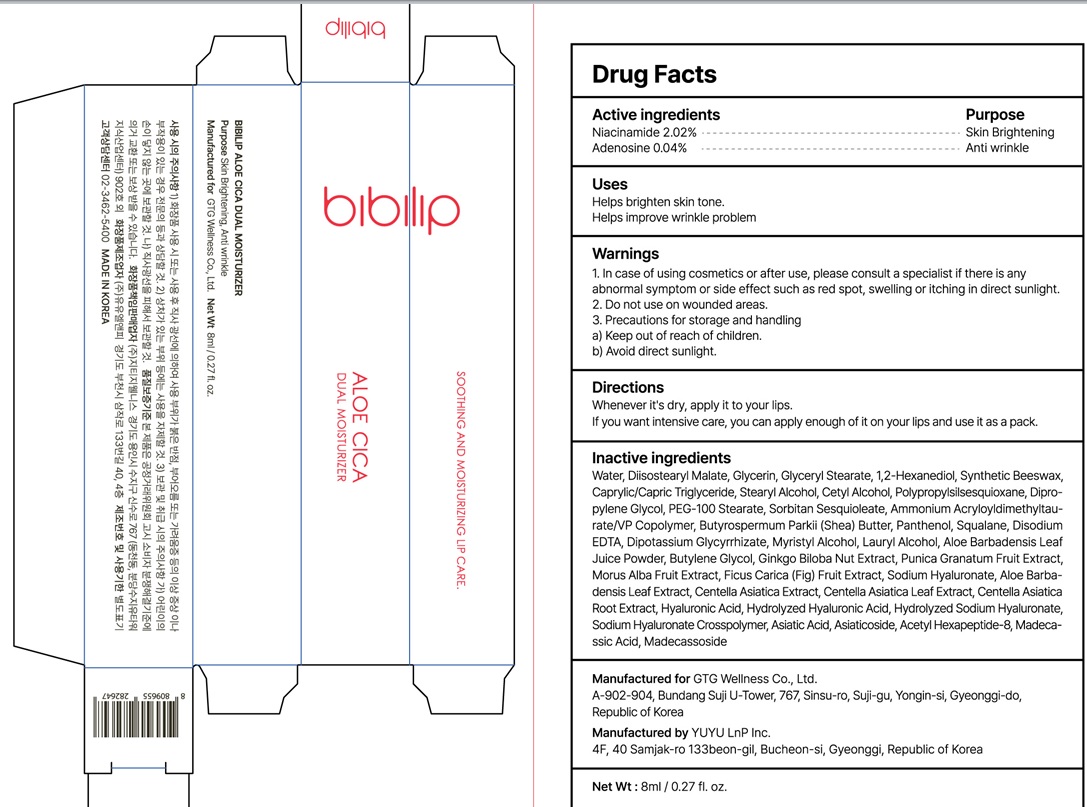 DRUG LABEL: BIBILIP ALOE CICA DUAL MOISTURIZER
NDC: 71080-0015 | Form: LIQUID
Manufacturer: GTG Wellness Co., Ltd.
Category: otc | Type: HUMAN OTC DRUG LABEL
Date: 20230525

ACTIVE INGREDIENTS: Niacinamide 0.16 g/8 mL; Adenosine 0.003 g/8 mL
INACTIVE INGREDIENTS: Water; Diisostearyl Malate

ACTIVE INGREDIENT

Active ingredients: Niacinamide 2.00%, Adenosine 0.04%

INACTIVE INGREDIENT

Inactive ingredients:

Water, Diisostearyl Malate, Beeswax, 1,2-Hexanediol, Cetyl Alcohol, Butyrospermum Parkii (Shea) Butter, Glyceryl Stearate, Squalane, Panthenol, Caprylic/Capric Triglyceride, Pantolactone, Madecassoside, Butylene Glycol, Dipotassium Glycyrrhizate, Hydroxypropyl Bispalmitamide MEA, Aloe Barbadensis Leaf Extract, Althaea Rosea Root Extract, Ficus Carica (Fig) Fruit Extract, Punica Granatum Fruit Extract, Morus Alba Fruit Extract, Ginkgo Biloba Nut Extract, Ammonium Acryloyldimethyltaurate/VP Copolymer,
PEG-100 Stearate, Hydrolyzed Hyaluronic Acid, Aloe Barbadensis Leaf Juice Powder, Fragrance

PURPOSE

Purpose: Skin Brightening, Anti wrinkle

WARNINGS

1. In case of using cosmetics or after use, please consult a specialist if there is any abnormal symptom or side effect such as red spot, swelling or itching in direct sunlight.
2. Do not use on wounded areas.
3. Precautions for storage and handling
a) Keep out of reach of children.
b) Avoid direct sunlight.

KEEP OUT OF REACH OF CHILDREN

Uses

Helps brighten skin tone.
Helps improve wrinkle problem.

Directions

After washing your face, apply a suitable amount to your lips in the next step of skincare.
If you want intensive care, you can apply enough of it on your lips and use it as a pack.